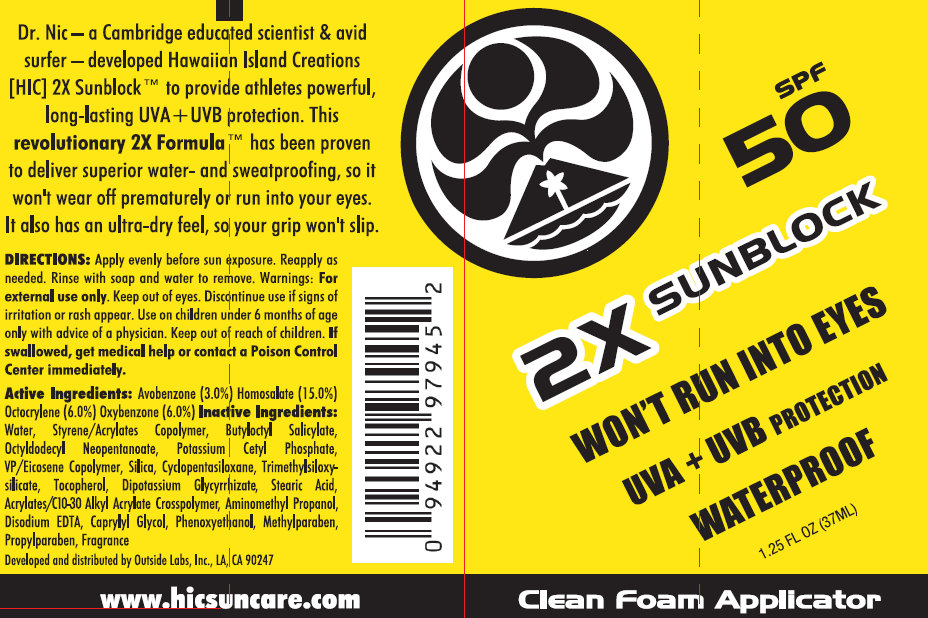 DRUG LABEL: 2X Sunblock SPF 50
NDC: 76174-120 | Form: LIQUID
Manufacturer: Nupur Formulations Inc
Category: otc | Type: HUMAN OTC DRUG LABEL
Date: 20110428

ACTIVE INGREDIENTS: AVOBENZONE 3 mL/100 mL; HOMOSALATE 15 mL/100 mL; OCTOCRYLENE 6 mL/100 mL; OXYBENZONE 6 mL/100 mL
INACTIVE INGREDIENTS: WATER; BUTYLOCTYL SALICYLATE; OCTYLDODECYL NEOPENTANOATE; POTASSIUM CETYL PHOSPHATE; SILICON DIOXIDE; CYCLOMETHICONE 5; ALPHA-TOCOPHEROL; GLYCYRRHIZINATE DIPOTASSIUM; STEARIC ACID; C10-30 CHOLESTEROL/LANOSTEROL ESTERS; AMINOMETHYLPROPANOL; EDETATE DISODIUM; CAPRYLYL GLYCOL; PHENOXYETHANOL; METHYLPARABEN; PROPYLPARABEN

Scape SPF 50+ Athlete Sunblock CleanFoam

Dr. Nic Martens - a biochemist and athlete - developed SCAPE Athlete Sunblock to address the protection and performance needs of athletes. The formula's engineered polymers bond to skin for long lasting waterproofing and sweatproofing that won't run into your eyes. SCAPE Athlete Sunblock provides superior UVA + UVB protection in a non-greasy, noncomedogenic formula that allows you to maintain optimal core body temperature and lets your skin breathe naturally.

DOSAGE AND ADMINISTRATION

Directions: Apply evenly to cool, dry skin 10 minutes before activity or sun exposure. Reapply as needed. Rinse with soap and water to remove.

WARNINGS

Warnings: For external use only. Keep out of eyes. Discontinue use if signs of irritation or rash appear. Use on children under 6 months of age only with advice of a physician. Keep out of reach of children. If swallowed, get medical help or contact a Poison Control Center immediately.

Active Ingredients:

Avobenzone 3%, Homosalate 15%, Octocrylene 6%, Oxybenzone 6%

Inactive Ingredients:

Water (Aqua), Styrene/Acrylates Copolymer, Butyloctyl Salicylate,Octyldodecyl Neopentanoate, Potassium Cetyl Phosphate, VP/Eicosene Copolymer, Silica,Cyclopentasiloxane, Trimethylsiloxysilicate, Tocopherol, Dipotassium Glycyrrhizate, Stearic Acid, Acrylates/C10-30 Alkyl Acrylate Crosspolymer, Aminomethyl Propanol, Disodium EDTA, Caprylyl Glycol, Phenoxyethanol, Methylparaben, Propylparaben, Fragrance (Parfum)

SCAPElabs.com

Developed and distributed by:

Outside Labs, Inc. LA CA 90247

PACKAGE LABEL

FROM THE LAB OF DR. NIC MARTENS

SCAPE

ATHLETE SUNBLOCK

UVA + UVB

SPF 50+

WON'T RUN INTO EYES

HIGH ENDURANCE

WATERPROOF AND SWEATPROOF

CleanFoam Applicator

1.25 FL OZ (37ML)